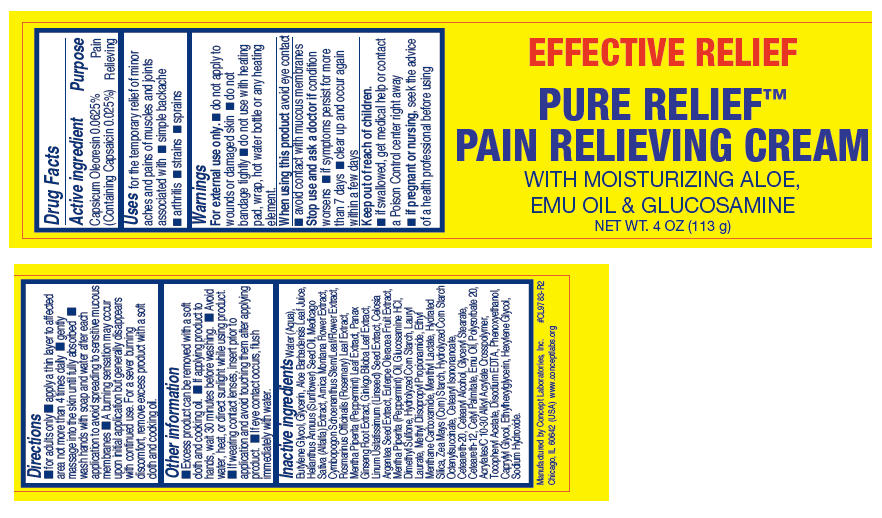 DRUG LABEL: Pure Relief
NDC: 64058-356 | Form: CREAM
Manufacturer: Concept Laboratories, Inc.
Category: otc | Type: HUMAN OTC DRUG LABEL
Date: 20170227

ACTIVE INGREDIENTS: Capsaicin 2.5 mg/1 g
INACTIVE INGREDIENTS: Water; ALOE VERA LEAF; METHYL DIISOPROPYL PROPIONAMIDE; ETHYL MENTHANE CARBOXAMIDE; MENTHYL LACTATE, (-)-; LAURYL LAURATE; STARCH, CORN; HYDRATED SILICA; GLUCOSAMINE HYDROCHLORIDE; DIMETHYL SULFONE; GLYCERIN; SUNFLOWER OIL; ALFALFA; ARNICA MONTANA FLOWER; CYMBOPOGON SCHOENANTHUS TOP; ROSEMARY; MENTHA PIPERITA LEAF; ASIAN GINSENG; GINKGO; FLAX SEED; CELOSIA ARGENTEA SEED; ACAI; EDETATE DISODIUM; EMU OIL; POLYSORBATE 20; .ALPHA.-TOCOPHEROL ACETATE; BUTYLENE GLYCOL; PHENOXYETHANOL; CAPRYLYL GLYCOL; Ethylhexylglycerin; Hexylene Glycol; CETEARYL ISONONANOATE; POLYOXYL 20 CETOSTEARYL ETHER; CETOSTEARYL ALCOHOL; GLYCERYL MONOSTEARATE; CETEARETH-12; CETYL PALMITATE; PEPPERMINT OIL; SODIUM HYDROXIDE

Pure Relief™

Drug Facts

Active ingredient

Capsicum Oleoresin 0.0625% (Containing Capsaicin 0.025%)

Purpose

Pain Relieving

Uses

for the temporary relief of minor aches and pains of muscles and joints associated with

- simple backache
- arthritis
- strains
- sprains

Warnings

For external use only.

- do not apply to wounds or damaged skin
- do not bandage tightly
- do not use with heating pad, wrap, hot water bottle or any heating element.

When using this product avoid eye contact

- avoid contact with mucous membranes

Stop use and ask a doctor if condition worsens

- if symptoms persist for more than 7 days
- clear up and occur again within a few days

Keep out of reach of children.

- if swallowed, get medical help or contact a Poison Control center right away

PREGNANCY OR BREAST FEEDING

- if pregnant or nursing, seek the advice of a health professional before using

Directions

- for adults only
- apply a thin layer to affected area not more than 4 times daily
- gently massage into the skin until fully absorbed
- wash hands with soap and water after each application to avoid spreading to sensitive mucous membranes

Other information

- Excess product can be removed with a soft cloth and cooking oil.
- If applying product to hands, wait 30 minutes before washing.
- Avoid water, heat, or direct sunlight while using product.
- If wearing contact lenses, insert prior to application and avoid touching them after applying product.
- If eye contact occurs, flush immediately with water.

Inactive ingredients

Water (Aqua), Butylene Glycol, Glycerin, Aloe Barbadensis Leaf Juice, Helianthus Annuus (Sunflower) Seed Oil, Medicago Sativa (Alfalfa) Extract, Arnica Montana Flower Extract, Cymbopogon Schoenanthus Stem/Leaf/Flower Extract, Rosmarinus Officinalis (Rosemary) Leaf Extract, Mentha Piperita (Peppermint) Leaf Extract, Panax Ginseng Root Extract, Ginkgo Biloba Leaf Extract, Linum Usitatissimum (Linseed) Seed Extract, Celosia Argentea Seed Extract, Euterpe Oleracea Fruit Extract, Mentha Piperita (Peppermint) Oil, Glucosamine HCl, Dimethyl Sulfone, Hydrolyzed Corn Starch, Lauryl Laurate, Methyl Diisopropyl Propionamide, Ethyl Menthane Carboxamide, Menthyl Lactate, Hydrated Silica, Zea Mays (Corn) Starch, Hydrolyzed Corn Starch Octenylsuccinate, Cetearyl Isononanoate, Ceteareth-20, Cetearyl Alcohol, Glyceryl Stearate, Ceteareth-12, Cetyl Palmitate, Emu Oil, Polysorbate 20, Acrylates/C 10-30 Alkyl Acrylate Crosspolymer, Tocopheryl Acetate, Disodium EDTA, Phenoxyethanol, Caprylyl Glycol, Ethylhexylglycerin, Hexylene Glycol, Sodium Hydroxide.

Manufactured by Concept Laboratories, Inc.
Chicago, IL 60642 (USA) www.conceptlabs.org
#CL9783-R2

PRINCIPAL DISPLAY PANEL - 113 g Jar Label

EFFECTIVE RELIEF

PURE RELIEF™
PAIN RELIEVING CREAM

WITH MOISTURIZING ALOE,
EMU OIL & GLUCOSAMINE

NET WT. 4 OZ (113 g)